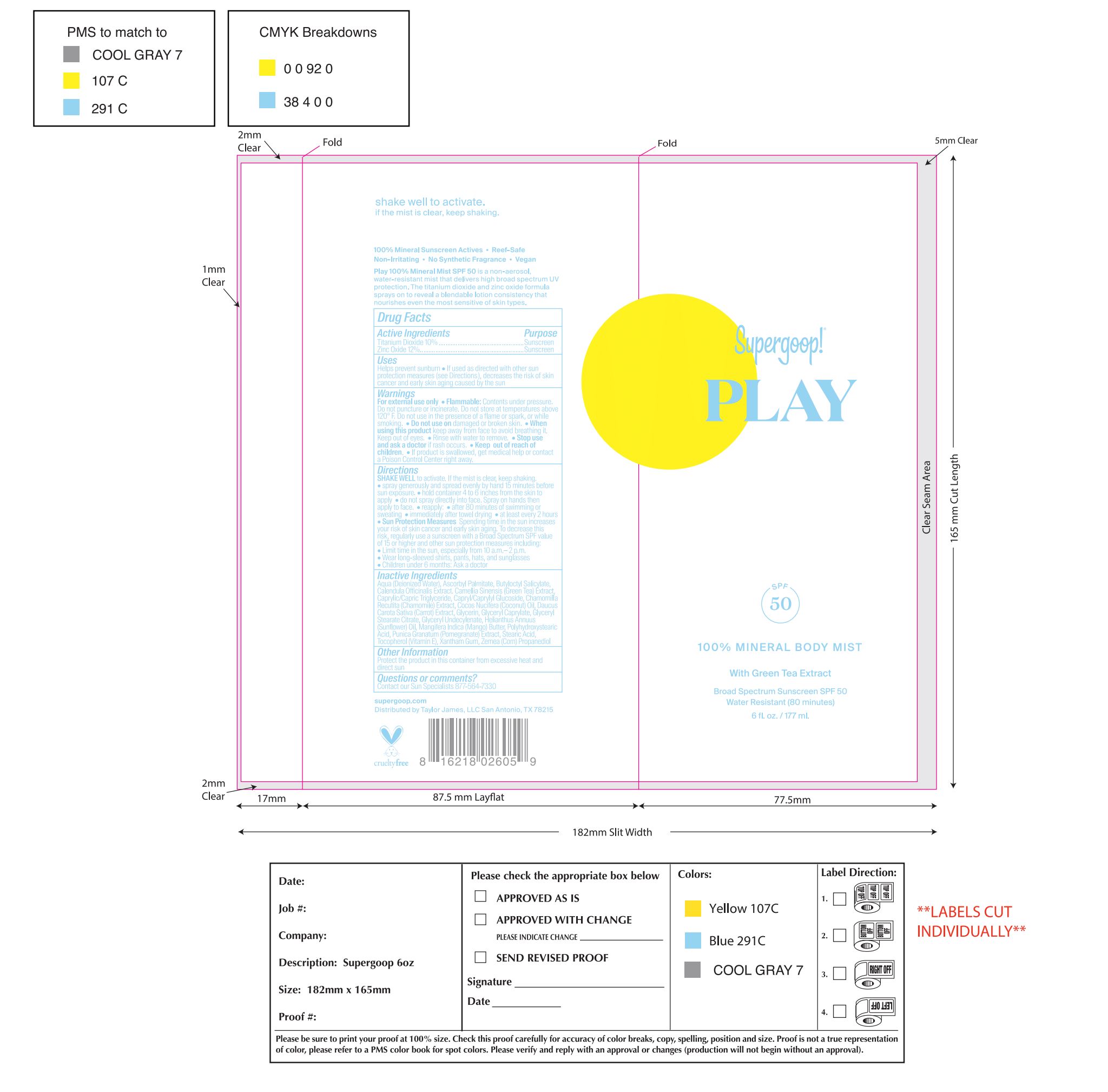 DRUG LABEL: Mineral Sunscreen SPF 30
NDC: 75936-510 | Form: SPRAY
Manufacturer: Supergoop, LLC
Category: otc | Type: HUMAN OTC DRUG LABEL
Date: 20221011

ACTIVE INGREDIENTS: ZINC OXIDE 12 g/100 mL
INACTIVE INGREDIENTS: FILIPENDULA ULMARIA ROOT; HEPTYL UNDECYLENATE; HYDROLYZED JOJOBA ESTERS (ACID FORM); MELISSA OFFICINALIS LEAF; METHYL DIHYDROABIETATE; NASTURTIUM OFFICINALE FLOWERING TOP; FILIPENDULA ULMARIA FLOWER; WATER; ALOE VERA LEAF; BENTONITE; BUTYLOCTYL SALICYLATE; CALENDULA OFFICINALIS FLOWER; CAPRYLHYDROXAMIC ACID; CAPRYLYL GLYCOL; GLYCERIN; SAFFLOWER OIL; CETOSTEARYL ALCOHOL; CHAMOMILE; COCO GLUCOSIDE; SUNFLOWER OIL

Mineral Sunscreen Mist SPF 30

Active Ingredients Purpose

Zinc Oxide 12.0% ..................................... Sunscreen

Uses

- Helps prevent sunburn
- If used as directed with other sun protection measures (see Directions), decreases the risk of skin cancer and early skin aging caused by the sun

Keep out of reach of children

Stop use and ask a doctor is rash occurs

Warnings

- For external use only
- Flammable: Contents under pressure. Do not punture or incinerate. Do not store at temperatures above 120 F. Do not use in the precesne of a flame or spark, or while smoking
- Do not use on damaged or broken skin
- When using this product keep out of eyes
- Rinse with water to remove
- Keep out of reach of children
- If swallowed, get medical help or contact a Poison Control Center right away

Directions

SHAKE WELL to activate. If the mist is clear, keep shaking.

- Apply liberally 15 minutes before sun exposure
- Reapply:

- after 80 minutes of swimming or sweating

- immediately after towel drying

- at least every 2 hours whem exposed to sunlight

- Children un 6 months: Ask a doctor

Sun Protection Measures. Spending time in the sun increases your risk of skin cancer and early skin aging. To decrease this risk, regularly use a sunscreen with a Broad Spectrum SPF value of 15 or higher and other sun protection measures including:

- Limit time in the sun epsecially from 10 a.m. - 2 p.m.
- Wear long-sleeved shirts, pants, hats, and sunglasses

INACTIVE INGREDIENT

Aloe Barbadensis Leaf Juice, Bentonite, Butyloctyl Salicylate, Calendula Officinalis Flower Extract, Caprylhydroxamic Acid, Caprylyl Glycol, Carthamus Tinctorius (Safflower) Seed Oil, Cetearyl Alcohol, Chamomilla Recutita (Matricaria) Flower Extract, Coco Glucoside, Glycerin, Helianthus Annuus (Sunflower) Seed Oil, Heptyl Undecylenate, Jojoba Esters, Melissa Officinalis Leaf Extract, Methyl Dihydroabietate, Nasturtium Officinale Flower/Leaf Extract, Spiraea Ulmaria Flower Extract, Water

PACKAGE LABEL

Supergoop!

Play

SPF 30

100% Mineral Body Mist

with Marigold Extract

Broad Spectrum Sunscreen SPF 30

Water Resistant (80 minutes)

6 fl. oz. / 177 mL.